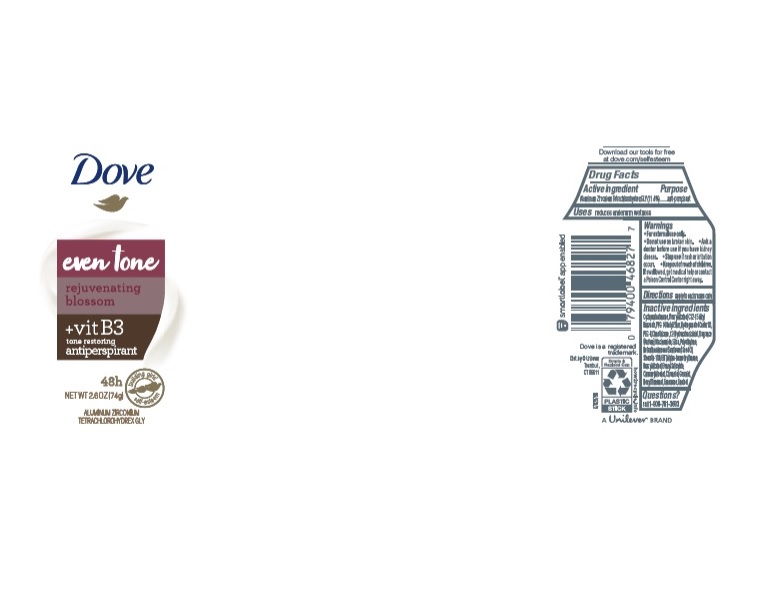 DRUG LABEL: Dove
NDC: 64942-1667 | Form: STICK
Manufacturer: Conopco Inc. d/b/a/ Unilever
Category: otc | Type: HUMAN OTC DRUG LABEL
Date: 20221207

ACTIVE INGREDIENTS: ALUMINUM ZIRCONIUM TETRACHLOROHYDREX GLY 11.4 g/100 g
INACTIVE INGREDIENTS: ISOMETHYL-.ALPHA.-IONONE; CINNAMYL ALCOHOL; LIMONENE, (+)-; HIGH DENSITY POLYETHYLENE; CYCLOMETHICONE 5; HYDROGENATED CASTOR OIL; BUTYLATED HYDROXYTOLUENE; PPG-14 BUTYL ETHER; STEARYL ALCOHOL; SUNFLOWER OIL; SILICON DIOXIDE; ALKYL (C12-15) BENZOATE; DIMETHICONE; STEARETH-100; POLYETHYLENE GLYCOL 400; .BETA.-CITRONELLOL, (R)-; LINALOOL, (+/-)-; BENZYL ALCOHOL; BENZYL SALICYLATE; 12-HYDROXYSTEARIC ACID; GERANIOL; .ALPHA.-HEXYLCINNAMALDEHYDE; NIACINAMIDE

Dove Even Tone Rejuvenating Blossom Antiperspirant

DOVE EVEN TONE REJUVENATNG BLOSSOM ANTIPERSPIRANT - aluminum zirconium tetrachlorohydrex gly stick

Dove Even Tone Rejuvenating Blossom Antiperspirant

Drug Facts

Active ingredient

Aluminum Zirconium Tetrachlorohydrex GLY (11.4 %)

Purpose

antiperspirant

Uses

• reduces underarm wetness

Warnings

• For external use only.
• Do not use on broken skin .
• Ask a doctor before use if you have kidney disease.
• Stop use if rash or irritation occurs.

• Keep out of reach of children.

If swallowed, get medical help or contact a Poison Control Center right away.

Directions

apply to underarms only

Inactive ingredients

Cyclopentasiloxane, Stearyl Alcohol, C12-15 Alkyl Benzoate, PPG-14 Butyl Ether, Hydrogenated Castor Oil, PEG-8, Dimethicone, 12-Hydroxystearic Acid, Fragrance (Parfum), Niacinamide, Silica, Polyethylene, Helianthus Annuus (Sunflower) Seed Oil, Steareth-100, BHT, Alpha-Isomethyl Ionone, Benzyl Alcohol, Benzyl Salicylate, Cinnamyl Alcohol, Citronellol, Geraniol, Hexyl Cinnamal, Limonene, Linalool.

Questions?

Call toll-free 1-800-761-3683